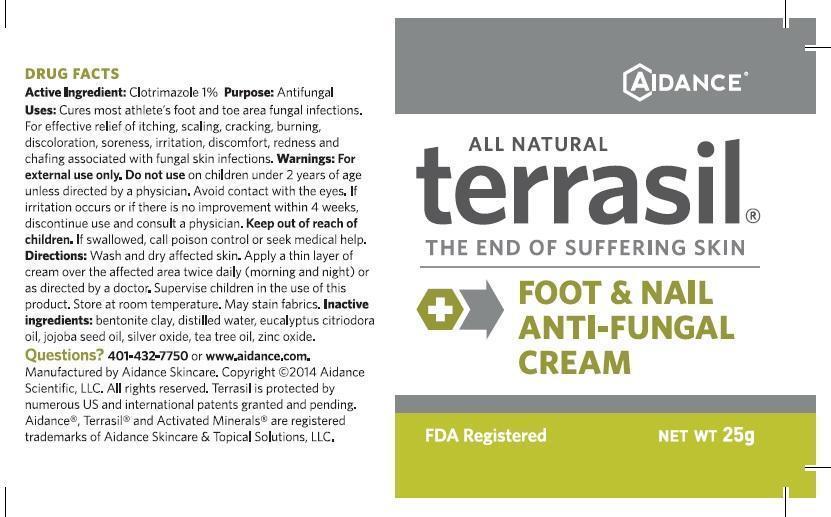 DRUG LABEL: Terrasil Foot and Nail Anti-Fungal
NDC: 24909-125 | Form: CREAM
Manufacturer: Aidance Skincare & Topical Solutions, LLC
Category: otc | Type: HUMAN OTC DRUG LABEL
Date: 20140626

ACTIVE INGREDIENTS: CLOTRIMAZOLE 1.0 g/100 g
INACTIVE INGREDIENTS: BENTONITE; EUCALYPTUS OIL; JOJOBA OIL; SILVER OXIDE; TEA TREE OIL; WATER; ZINC OXIDE

Drug Facts

Active Ingredient

Clotrimazole 1%

Purpose

Antifungal

Uses

Cures most athlete’s foot and toe area fungal infections. For effective relief of itching,
scaling, cracking, burning, discoloration, soreness, irritation, discomfort, redness and chafing
associated with fungal skin infections.

Warnings

For external use only. Do not use on children under 2 years of age unless directed by
a physician. Avoid contact with the eyes. If irritation occurs or if there is no improvement within 4
weeks, discontinue use and consult a physician.

Keep out of reach of children.

If swallowed, call poison control or seek medical help.

Directions

Wash and dry affected skin. Apply a thin layer of cream over the affected area
twice daily (morning and night) or as directed by a doctor. Supervise children in the use of
this product. Store at room temperature. May stain fabrics.

Inactive Ingredients

bentonite clay, distilled water, eucalyptus citriodora oil, jojoba seed oil, silver oxide, tea tree oil, zinc oxide.

Questions?401-432-7750 or www.Aidance.com

PRINCIPAL DISPLAY PANEL - 25g Bottle

ALL NATURAL

terrasil

THE END OF SUFFERING SKIN

FOOT & NAIL

ANTI-FUNGAL

CREAM